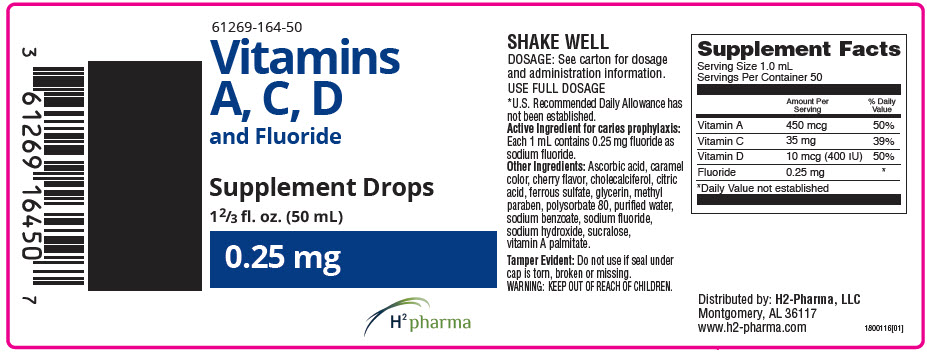 DRUG LABEL: Vitamins A, C, D and Fluoride Drops
NDC: 61269-164 | Form: SOLUTION/ DROPS
Manufacturer: H2-Pharma, LLC
Category: other | Type: DIETARY SUPPLEMENT
Date: 20250915

ACTIVE INGREDIENTS: VITAMIN A PALMITATE 450 ug/1 mL; ASCORBIC ACID 35 mg/1 mL; CHOLECALCIFEROL 10 ug/1 mL; SODIUM FLUORIDE 0.25 mg/1 mL
INACTIVE INGREDIENTS: CARAMEL; CITRIC ACID MONOHYDRATE; FERROUS SULFATE; CHERRY; GLYCERIN; METHYLPARABEN; POLYSORBATE 80; WATER; SODIUM BENZOATE; SODIUM HYDROXIDE; SUCRALOSE

Vitamins A, C, D and Fluoride Drops

STATEMENT OF IDENTITY

Supplement Facts
Serving Size 1.0 mL
Servings Per Container 50
 | Amount Per Serving | % Daily Value
Vitamin A | 1500 IU | 60%
Vitamin C | 35 mg | 88%
Vitamin D | 400 IU | 100%
Fluoride | 0.25 mg | [Daily Value not established]

Active ingredient for caries prophylaxis: Fluoride as sodium fluoride.

Other ingredients: Ascorbic acid, caramel color, cholecalciferol, citric acid, ferrous sulfate, flavor, glycerin, methyl paraben, polysorbate 80, purified water, sodium benzoate, sodium hydroxide, sodium fluoride, sucralose, vitamin A palmitate.

CLINICAL PHARMACOLOGY

It is well established that fluoridation of the water supply (1 ppm fluoride) during the period of tooth development leads to a significant decrease in the incidence of dental caries. Hydroxyapatite is the principal crystal for all calcified tissue in the human body. The fluoride ion reacts with the hydroxyapatite in the tooth as it is formed to produce the more caries-resistant crystal, fluorapatite. The reaction may be expressed by the equation:

Ca10(PO4)6(OH)2+2F^− -> Ca10(PO4)6F2+2OH^−

(Hydroxyapatite)

(Fluorapatite)

Three stages of fluoride deposition in tooth enamel can be distinguished: 1. Small amounts (reflecting the low levels of the fluoride in tissue fluids) are incorporated into the enamel crystals while they are being formed. 2. After enamel has been laid down, fluoride deposition continues in the surface enamel. Diffusion of fluoride from the surface inward is apparently restricted. 3. After eruption, the surface enamel acquires fluoride from water, food, supplementary fluoride and smaller amounts from salvia.

Supplementation of the diet with Vitamins A, C, D and Fluoride 0.25 mg Drops also provides fluoride for caries prophylaxis. The American Academy of Pediatrics recommends that children up to age 16, in areas where drinking water contains less than optimal levels of fluoride, receive daily fluoride supplementation. Vitamins A, C, D and Fluoride 0.25 mg Drops provide fluoride in drop form for infants and young children 6 months to 3 years of age, in areas where the drinking water contains less than 0.3 ppm of fluoride, and for children ages 3-6 years, in areas where the drinking water contains 0.3 through 0.6 ppm of fluoride. Each 1.0 mL supplies sodium fluoride (0.25 mg fluoride) plus three basic vitamins. The American Academy of Pediatrics recommends that infants and young children 6 months to 3 years of age, in areas where the drinking water contains less than 0.3 ppm of fluoride; and for children ages 3-6 years, in areas where the drinking water contains 0.3 through 0.6 ppm of fluoride, receive 0.25 mg of supplemental fluoride daily which is provided in a full dose (1 mL) of Vitamins A, C, D and Fluoride 0.25 mg Drops. A comprehensive 5 ½ year series of studies of the effectiveness of multivitamins and fluoride drops in caries protection has been published. Children in this continuing study lived in an area where the water supply contained only 0.05 ppm fluoride. The subjects were divided into two groups: one which used only the non-fluoride vitamin drops, and the other group used multivitamin-fluoride drops. The three year interim report showed 63% fewer carious surfaces in primary teeth and 43% fewer carious surfaces in permanent teeth of the children taking multivitamin-fluoride products. After four years, the studies continued to support the effectiveness of multivitamin-fluoride products, showing a reduction in carious surfaces of 68% in primary teeth and 46% in permanent teeth. Results at the end of the 5 ½ years further confirmed the previous findings and indicated that significant reductions in dental caries are apparent with the continued use of multivitamin-fluoride products. *These statements have not been evaluated by the Food and Drug Administration. This product is not intended to diagnose, treat, cure, or prevent any disease.

WARNINGS

As in the case of all medications, keep out of reach of children.

PRECAUTIONS

The suggested dose should not be exceeded since dental fluorosis may result from continued ingestion of large amounts of fluoride. When recommending vitamin fluoride products: 1. Determine the fluoride content of the drinking water. 2. Make sure the child is not receiving significant amounts of fluoride from other medications and swallowed toothpaste. 3. Periodically check to make sure that the child does not develop significant dental fluorosis. 4. Vitamins A, C, D and Fluoride Supplemental Drops 0.25 mg should be dispensed in the original plastic container, since contact with glass leads to instability and precipitation. (The amount of sodium fluoride in the 50 mL size is well below the maximum to be dispensed at one time according to recommendations of the American Dental Association.)

ADVERSE REACTIONS

Allergic rash or other idiosyncrasies have been rarely reported. To report SUSPECTED ADVERSE REACTIONS, contact H2-Pharma at 1-866-592-6438 or the FDA at 1-800-FDA-1088 or www.fda.gov/medwatch.

DOSAGE AND ADMINISTATION

1.0 mL daily or as directed by physician. May be dropped directly into the mouth with the enclosed dropper or mixed with cereal, fruit juice or other food.

HOW SUPPLIED

Vitamins A, C, D and Fluoride 0.25 mg Drops are available in 50 mL bottles with accompanying calibrated dropper.

RECOMMENDED STORAGE

Store at controlled room temperature, 20°-25°C (66°-77°F) [See USP Controlled Room Temperature]. After opening, store away from direct sunlight. Close tightly after each use. REFRIGERATION IS NOT REQUIRED.

TAMPER EVIDENT: Do not use if printed bottle seal around bottle cap is broken or missing.

HEALTH CLAIM

Distributed by: H2-Pharma, LLC
2010 Berry Chase Place, Montgomery, AL 36117
www.h2-pharma.com

PRINCIPAL DISPLAY PANEL - 50 mL Bottle Label

61269-164-50

Vitamins
A, C, D
and Fluoride

Supplement Drops

1⅔ fl. oz. (50 mL)

0.25 mg

H^2 pharma